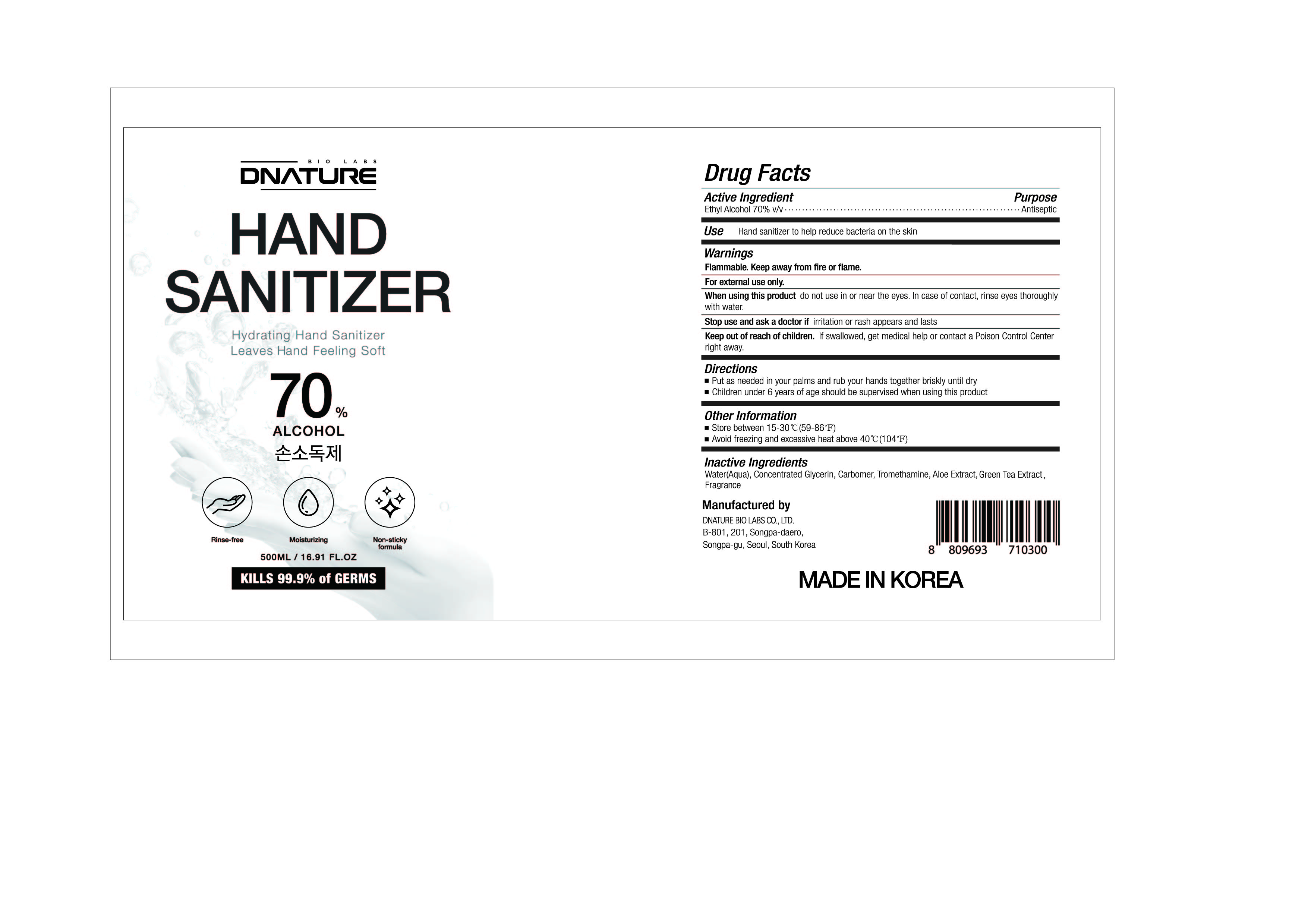 DRUG LABEL: DNATURE HAND SANITIZER
NDC: 74724-0003 | Form: GEL
Manufacturer: K.Boeun Pharmaceutical Co.,Ltd.
Category: otc | Type: HUMAN OTC DRUG LABEL
Date: 20200515

ACTIVE INGREDIENTS: ALCOHOL 70 g/100 mL
INACTIVE INGREDIENTS: GLYCERIN; WATER; CARBOMER HOMOPOLYMER, UNSPECIFIED TYPE; ALOE

Drug Facts

ACTIVE INGREDIENT

Alcohol

INACTIVE INGREDIENT

Water, Glycerin, Carbomer, Tromethamine, Aloe Extract, Green Tea Extract, Fragrance

PURPOSE

Antiseptic

KEEP OUT OF REACH OF THE CHILDREN

INDICATIONS AND USAGE

Store under 30°C (86°F)

WARNINGS

For external use only.

Flammable, keep away from fire or flame.

When using this product keep out of eyes. If contact with eyes occurs, rinse promptly and thoroughly with water.

Stop use and ask a doctor if significant irritation or sensitization develops.

Keep out of reach of children. If swallowed, get medical help or contact a Poison Control Center right away.

DOSAGE AND ADMINISTRATION

Put as needed in your palms and rub your hands together briskly until dry

Children under 6 years of age should be super vised when using this product